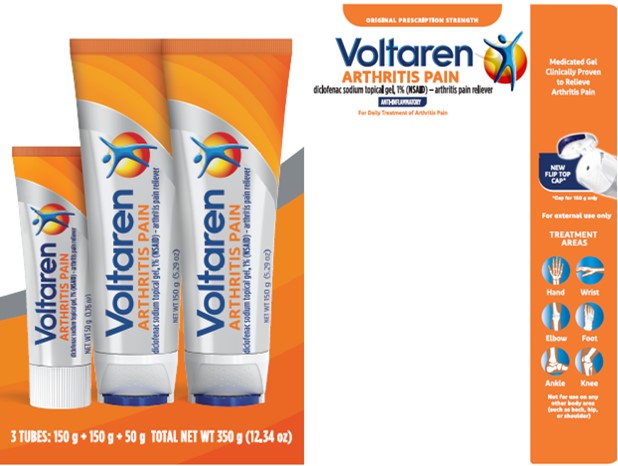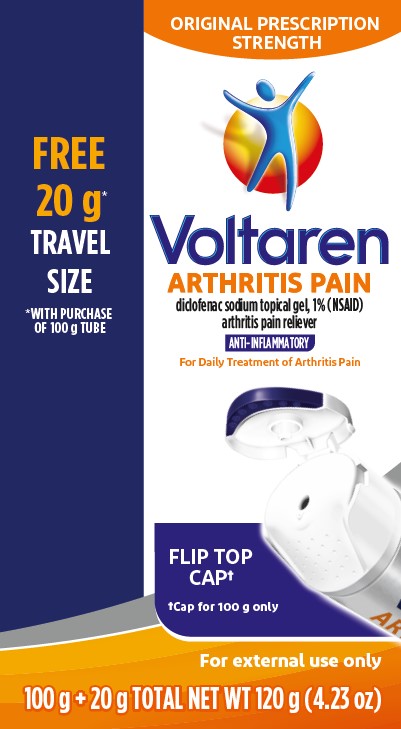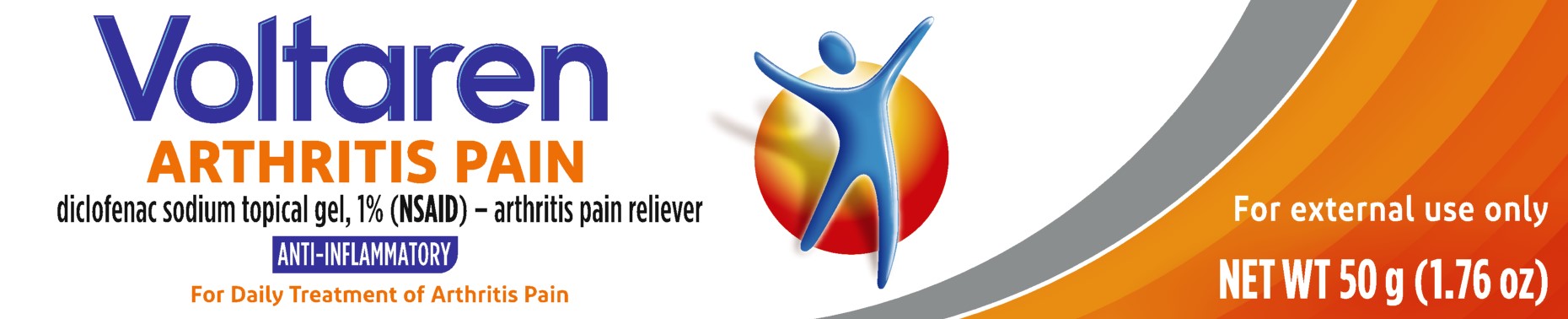 DRUG LABEL: Voltaren
NDC: 0067-8152 | Form: GEL
Manufacturer: Haleon US Holdings LLC
Category: otc | Type: HUMAN OTC DRUG LABEL
Date: 20250211

ACTIVE INGREDIENTS: DICLOFENAC SODIUM 10 mg/1 g
INACTIVE INGREDIENTS: AMMONIA; CARBOMER HOMOPOLYMER TYPE C (ALLYL PENTAERYTHRITOL CROSSLINKED); COCOYL CAPRYLOCAPRATE; ISOPROPYL ALCOHOL; MINERAL OIL; POLYOXYL 20 CETOSTEARYL ETHER; PROPYLENE GLYCOL; WATER

Drug Facts

Active ingredient

Diclofenac sodium (NSAID*) 1% (equivalent to 0.93% diclofenac)

*nonsteroidal anti-inflammatory drug

Purpose

Arthritis pain reliever

Uses

- for the temporary relief of arthritis pain ONLY in the following areas:
  - hand, wrist, elbow (upper body areas)
  - foot, ankle, knee (lower body areas)
- this product may take up to 7 days to work for arthritis pain; it is not for immediate relief. If no pain relief in 7 days, stop use.

Warnings

For external use only

Allergy alert: Diclofenac may cause a severe allergic reaction, especially in people allergic to aspirin.

Symptoms may include:

- hives
- asthma (wheezing)
- skin reddening
- blisters
- facial swelling
- shock
- rash

If an allergic reaction occurs, stop use and seek medical help right away.

Liver warning: This product contains diclofenac. Liver damage may occur if you apply

- more or for a longer time than directed
- when using other drugs containing diclofenac

Stomach bleeding warning: This product contains an NSAID, which may cause severe stomach bleeding. The chance is small but higher if you

- are age 60 or older
- have had stomach ulcers or bleeding problems
- take a blood thinning (anticoagulant) or steroid drug
- take other drugs containing prescription or nonprescription NSAIDs (aspirin, ibuprofen, naproxen, or others)
- have 3 or more alcoholic drinks every day while using this product
- apply more or for longer than directed

Heart attack and stroke warning: NSAIDs, except aspirin, increase the risk of heart attack, heart failure, and stroke. These can be fatal. The risk is higher if you use more than directed or for longer than directed.

Do not use

- if you have ever had an allergic reaction to any other pain reliever or to a fever reducer
- for strains, sprains, bruises or sports injuries. This product has not been shown to work for these types of injuries.
- right before or after heart surgery
- on more than 2 body areas at the same time
- in the eyes, nose or mouth

Ask a doctor before use if

- you have problems or serious side effects from taking pain relievers or fever reducers
- stomach bleeding warning applies to you
- you have a history of stomach problems, such as heartburn
- you have high blood pressure, heart disease, liver cirrhosis, kidney disease, asthma, or had a stroke
- you are taking a diuretic
- you are under age 18 years. It is not known if this drug works or is safe in children under age 18 years.

Ask a doctor or pharmacist before use if you are

- under a doctor’s care for any serious condition
- taking any other drug

When using this product

- avoid contact with eyes, nose, or mouth
- if eye contact occurs, rinse thoroughly with water

Stop use and ask a doctor if

- pain gets worse or lasts more than 21 days
- redness or swelling is present in the painful area
- fever occurs
- skin irritation occurs
- any new symptoms appear. These could be signs of a serious condition.
- you experience any of the following signs of stomach bleeding:
  - feel faint
  - have bloody or black stools
  - vomit blood
  - have stomach pain that does not get better
- you have symptoms of heart problems or stroke:
  - chest pain
  - trouble breathing
  - leg swelling
  - weakness in one part or side of body
  - slurred speech

If pregnant or breast-feeding,

ask a health professional before use. It is especially important not to use diclofenac at 20 weeks or later in pregnancy unless definitely directed to do so by a doctor because it may cause problems in the unborn child or complications during delivery.

Directions

Use up to 21 days unless directed by your doctor

Not for strains, sprains, bruises, or sports injuries. This product has not been shown to work for these types of injuries.

Daily | Per Dose
For your arthritis pain:; • Use 4 times per day every day • Do not use on more than 2 body areas at the same time | Use ENCLOSED DOSING CARD to measure a dose; • For each upper body area (hand, wrist, or elbow) – Squeeze out 2.25 inches (2 grams) • For each lower body area (foot, ankle or knee) – Squeeze out 4.5 inches (4 grams)

Read the enclosed User Guide for complete instructions:

- use only as directed
- do not use more than directed or for longer than directed
- apply only to clean, dry skin that does not have any cuts, open wounds, infections or rashes
- do not apply in same area as any other product
- do not apply with external heat such as heating pad
- do not apply a bandage over the treated area
- store ENCLOSED DOSING CARD with your Voltaren Arthritis Pain. The dosing card is
  re-usable.

Other information

- store at 20-25°C (68-77°F). Keep from freezing.
- read all product information before using. Keep the dosing card, this carton and accompanying User Guide for important information.

Inactive ingredients

carbomer homopolymer Type C, cocoyl caprylocaprate, fragrance, isopropyl alcohol, mineral oil, polyoxyl 20 cetostearyl ether, propylene glycol, purified water, strong ammonia solution

Questions or comments?

1-855-297-3031 www.voltarengel.com

Additional Information

ORIGINAL PRESCRIPTION STRENGTH

Medicated Gel Clinically Proven to Relieve Arthritis Pain

TREATMENT AREAS

Hand Wrist Elbow Foot Ankle Knee
Not for use on any other body area (such as back, hip, or shoulder)

Use Enclosed Dosing Card to Measure a Dose

Voltaren ARTHRITIS PAIN

diclofenac sodium topical gel, 1% (NSAID) – arthritis pain reliever

Dosing Card (NOT ACTUAL SIZE)

Read product User Guide before use

Not for immediate pain relief

Upper body dose 2.25 inches long (2 grams)

Lower body dose 4.5 inches long (4 grams)

How to Use:

- For arthritis pain only
- Use 4 times a day
- May take up to 7 days to work for your arthritis pain
- For use on no more than 2 body areas
- Use up to 21 days unless directed by your doctor
Screw Cap Tamper evident statement: Do not use if safety seal on tube nozzle is broken or missing.
Flip Cap Tamper evident statement: Do not use if plastic safety seals on sides of cap are broken or missing.

Principal Display Panel (50 g)

Voltaren

ARTHRITIS PAIN

diclofenac sodium topical gel, 1% (NSAID) - arthritis pain reliever

ANTI-INFLAMMATORY

For Daily Treatment of Arthritis Pain

For external use only

NET WT 50 g (1.76 oz)

Principal Display Panel (150 g + 150 g + 50 g)

ORIGINAL PRESCRIPTION STRENGTH

Voltaren

ARTHRITIS PAIN

diclofenac sodium topical gel, 1% (NSAID) - arthritis pain reliever

ANTI-INFLAMMATORY

For Daily Treatment of Arthritis Pain

Medicated Gel Clinically Proven to Relieve Arthritis Pain

NEW FLIP TOP CAP*

*Cap for 150 g only

For external use only

TREATMENT AREAS

Hand Wrist Elbow Foot Ankle Knee
Not for use on any other body area (such as back, hip, or shoulder)
3 TUBES: 150 g + 150 g + 50 g TOTAL NET WT 350 g (12.34 oz)

Principal Display Panel (100 g + 20 g)

FREE 20 g* TRAVEL SIZE

*WITH PURCHASE OF 100 g TUBE

ORIGINAL PRESCRIPTION STRENGTH

Voltaren

ARTHRITIS PAIN

Diclofenac sodium topical gel, 1% (NSAID) arthritis pain reliever

ANTI-INFLAMMATORY

For Daily Treatment of Arthritis Pain

FLIP-TOP CAP†

†Cap for 100 g only

For external use only

100 g + 20 g TOTAL NET WT 120 g (4.23 oz)